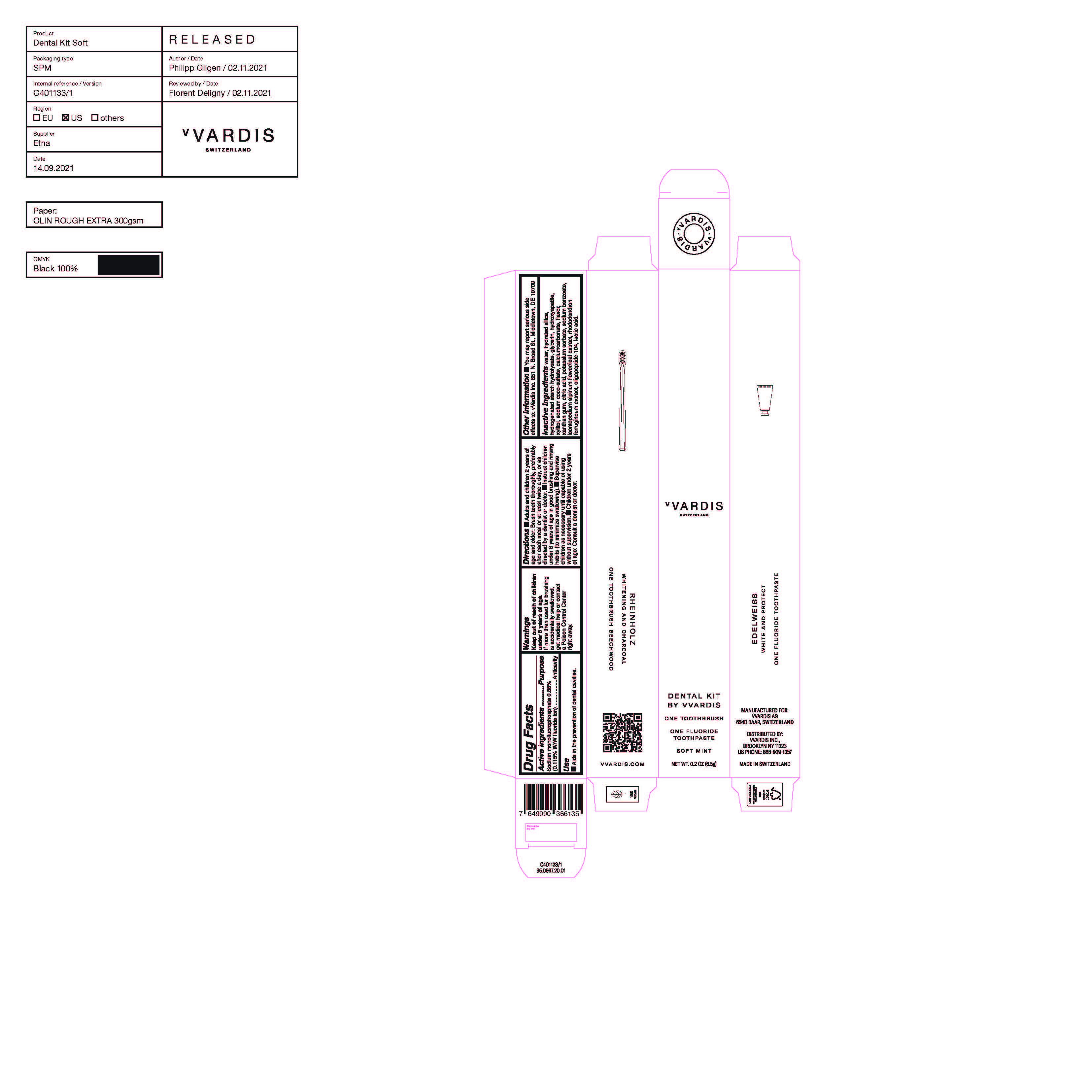 DRUG LABEL: Dental Kit Soft Mint
NDC: 82615-001 | Form: KIT | Route: DENTAL
Manufacturer: vVARDIS AG
Category: otc | Type: HUMAN OTC DRUG LABEL
Date: 20220307

ACTIVE INGREDIENTS: SODIUM MONOFLUOROPHOSPHATE 0.88 g/100 g
INACTIVE INGREDIENTS: XANTHAN GUM; POTASSIUM SORBATE; SODIUM BENZOATE; WATER; HYDRATED SILICA; HYDROGENATED STARCH HYDROLYSATE; TRIBASIC CALCIUM PHOSPHATE; XYLITOL; SODIUM COCO-SULFATE; CITRIC ACID MONOHYDRATE; LEONTOPODIUM ALPINUM FLOWERING TOP; CALCIUM CARBONATE; GLYCERIN; RHODODENDRON FERRUGINEUM WHOLE; LACTIC ACID

Dental Kit Soft Mint

Active Ingredients Purpose

Sodium monofluorophosphate 0.88% (0.115% W/V fluoride Ion) Anticavity

PURPOSE

Use - Aids in the prevention of dental cavities.

Keep out of reach of children under 6 years age.

Use
Aids in the prevention of dental cavities.

WARNINGS

Keep our of reach of children under 6 years of age. If more than used for brushing is accidentally swallowed, get medical help or contact a Poison Control Center right away.

Directions

Adults and children 2 years of age and older: Brush teeth thoroughly, preferably after each meal or at least twice a day, or as directed by a dentist or doctor.
Instruct children under 6 years of age in good brushing and rinsing habits (to minimize swallowing).
Supervise children as necessary until capable of using without supervision.
Children under 2 years of age: Consult a dentist or doctor.

Other Information

You may report serious side effects to : vVardis, Inc.

651 N. Broad St., Middletown, DE 19709

Inactive Ingredients

water, hydrated silica, hydrogenated strach hydrolysate, glycerin, hydroxyapatite, xylitol, sodium coco-sulfate, calcium carbonate, flavor, xanthan gum, citric acid, potasium sorbate, sodium benzoate, leontopodium alpinum flower/leaf extract, rhododendron ferrugineum extract, oligopeptide-104, lactic acid

PACKAGE LABEL

vVARDIS

Switzerland

Dental Kit by VVARDIS

One Toothbrush

One Fluoride toothpaste

Soft Mint

NET. WT. 0.2 OZ (6.5g)